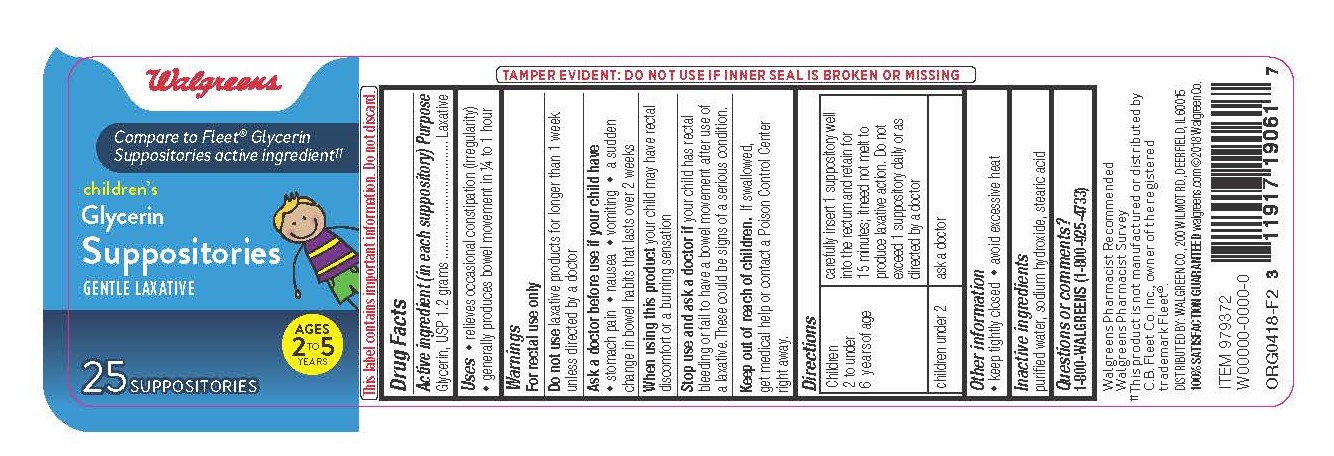 DRUG LABEL: Walgreens Children Glycerin

NDC: 0363-0440 | Form: SUPPOSITORY
Manufacturer: Walgreens
Category: otc | Type: HUMAN OTC DRUG LABEL
Date: 20221219

ACTIVE INGREDIENTS: GLYCERIN 83 g/100 g
INACTIVE INGREDIENTS: STEARIC ACID 8.5 g/100 g; SODIUM HYDROXIDE 1.2 g/100 g; WATER 7.3 g/100 g

Walgreens® Childern Glycerin Suppositories 25ct.

Active Ingredient

(in each suppository)
Glycerin, USP 1.2 grams

Uses

-relieves occasional constipation (irregularity)

-generally produces bowel movement in 1/4 to 1 hour

Warnings

For rectal use only

Do not use laxative products for longer than 1 week unless directed by a doctor

Ask a doctor before use if your child have

- stomach pain - nausea - vomiting - a sudden change in bowel habits that lasts over 2 weeks

When using this product your child may have rectal discomfort or a burning sensation

Stop use and ask a doctor if your child has rectal bleeding or fail to have a bowel movement after use of a laxative.

These could be signs of a serious condition.

Keep out of reach of children.

If swallowed, get medical help or contact a Poison Control Center right away.

Directions

children 2 to under 6 years...........carefully insert 1 suppository well into the rectum and retain for 15 minutes; it need not melt to produce laxative action. Do not exceed 1 suppository daily or as directed by a doctor.

children under 2 years..................ask a doctor

Other information

-keep tightly closed

-avoid excessive heat

Inactive ingredients

purified water, sodium hydroxide, stearic acid

Purpose

Laxative